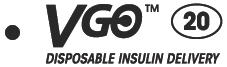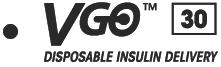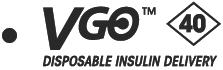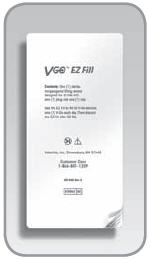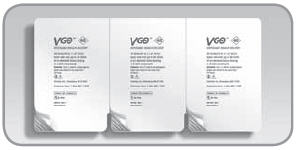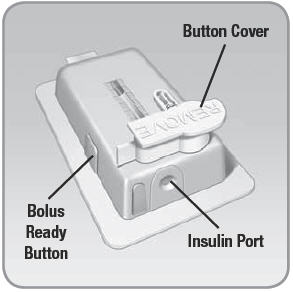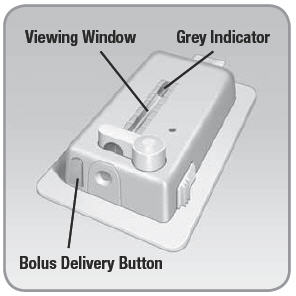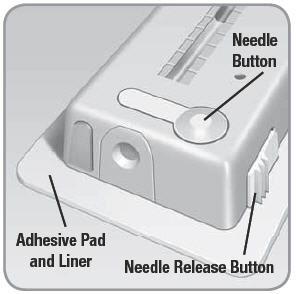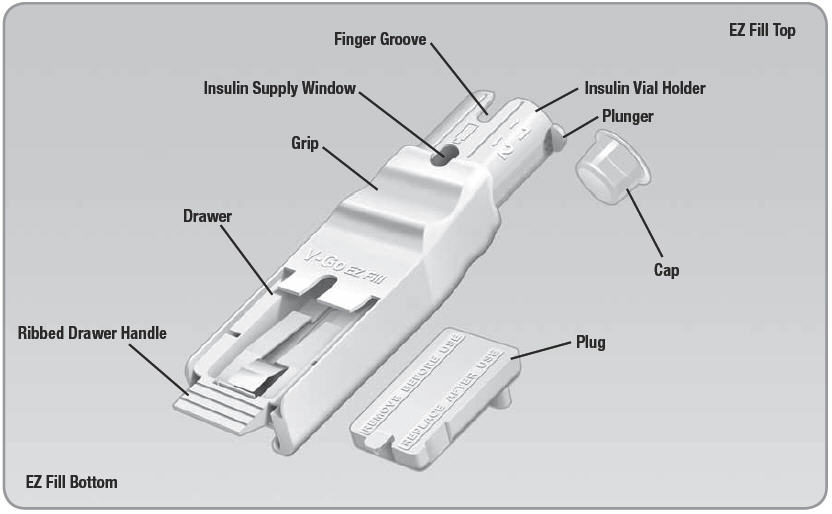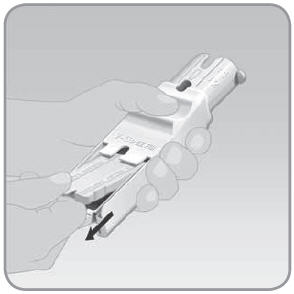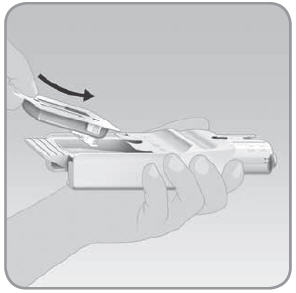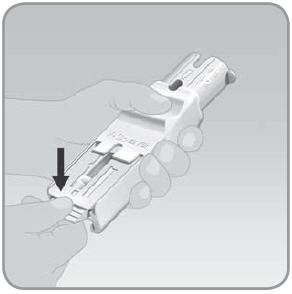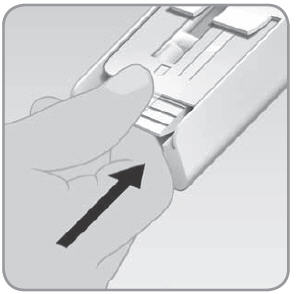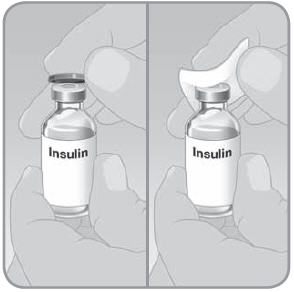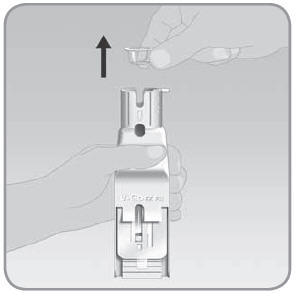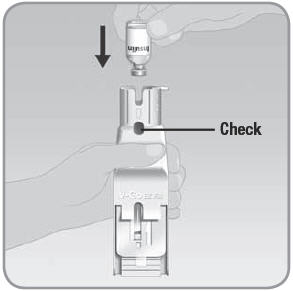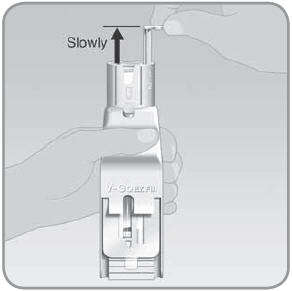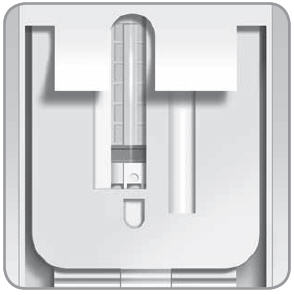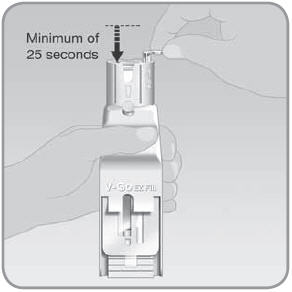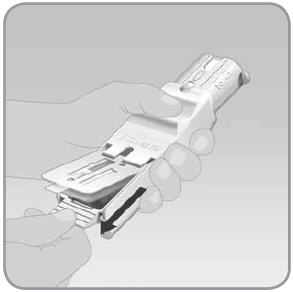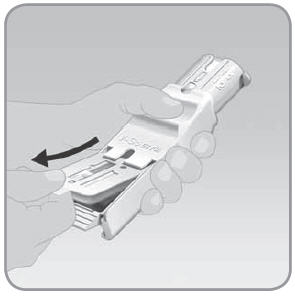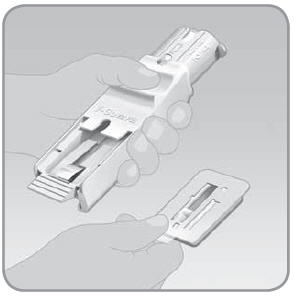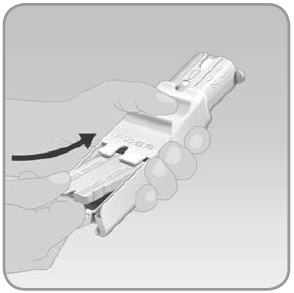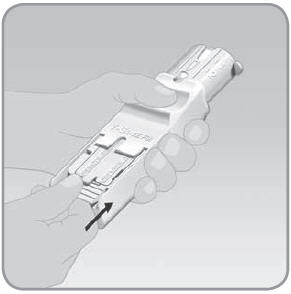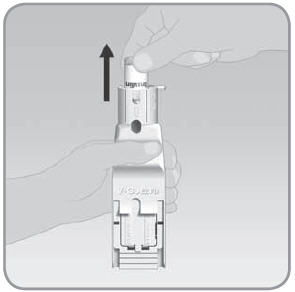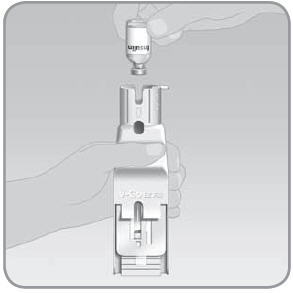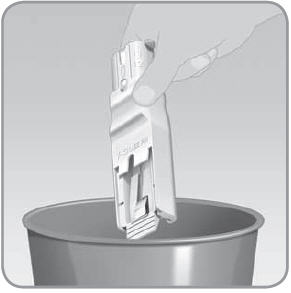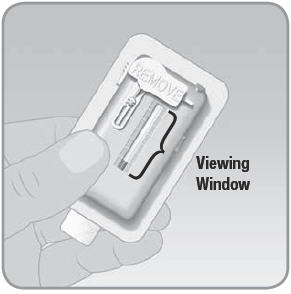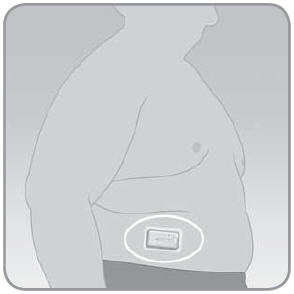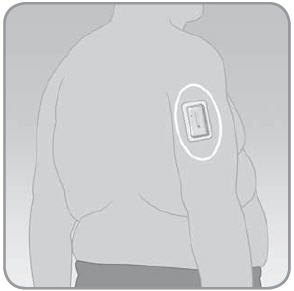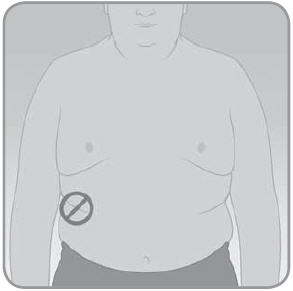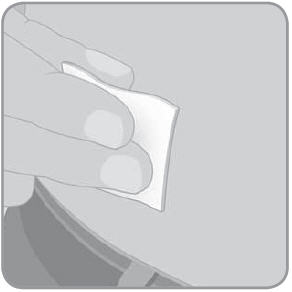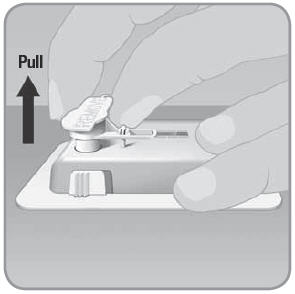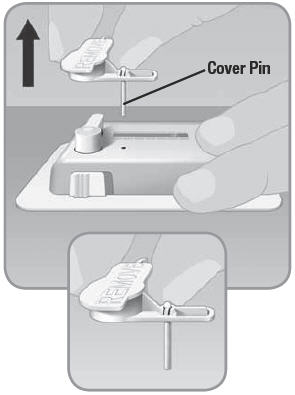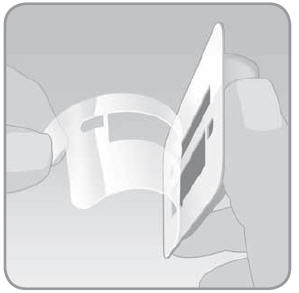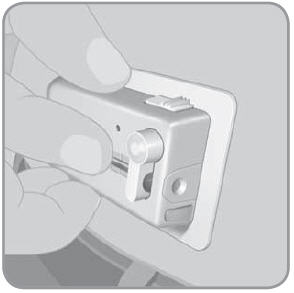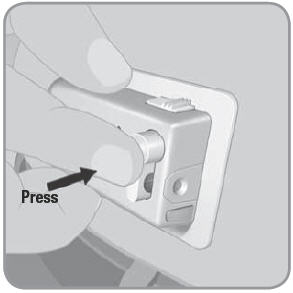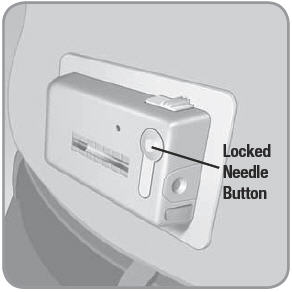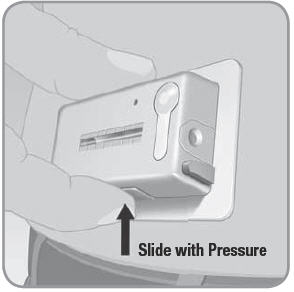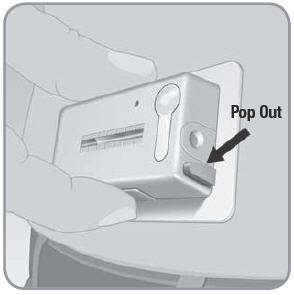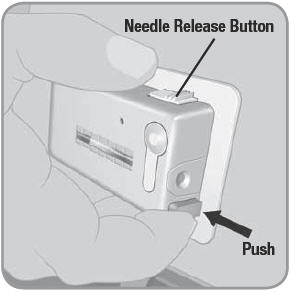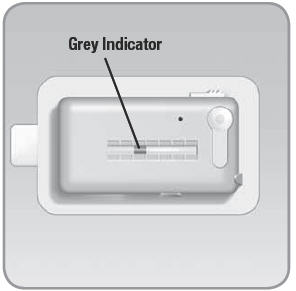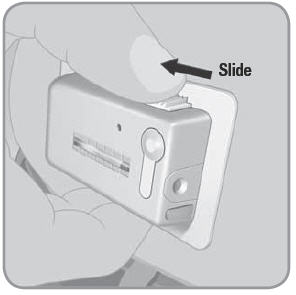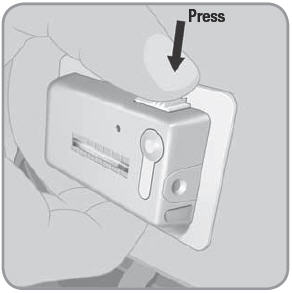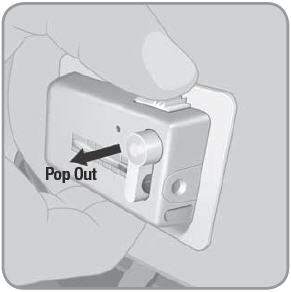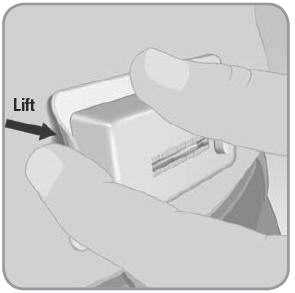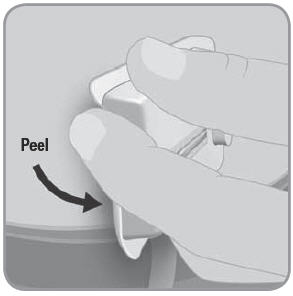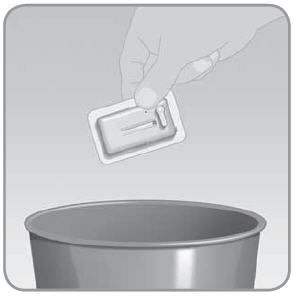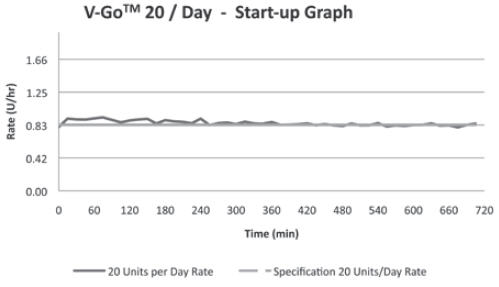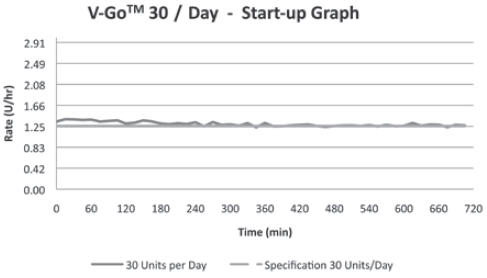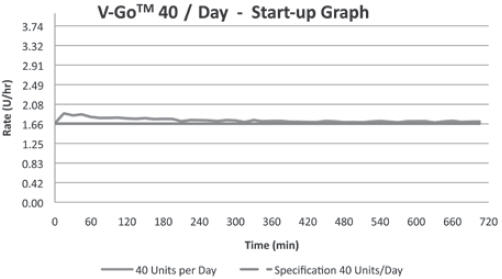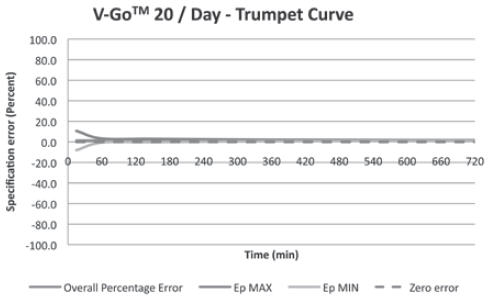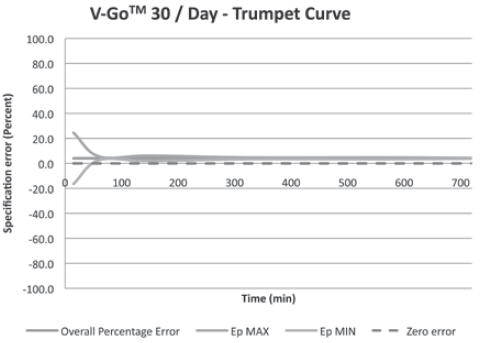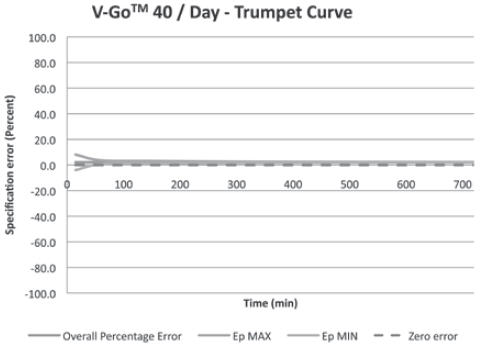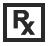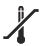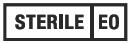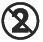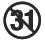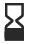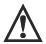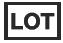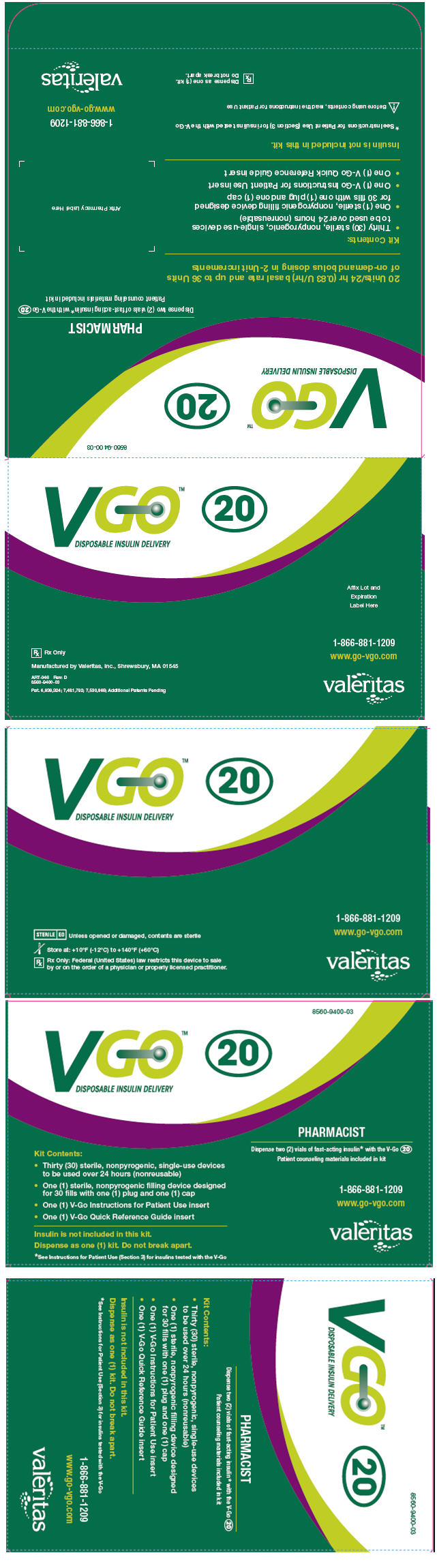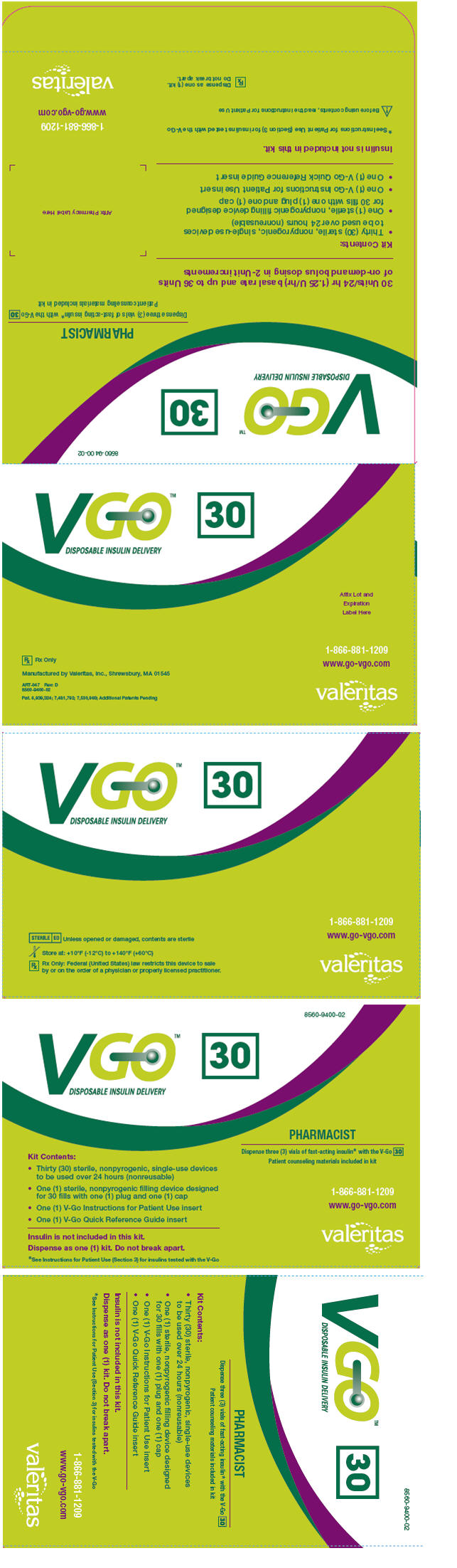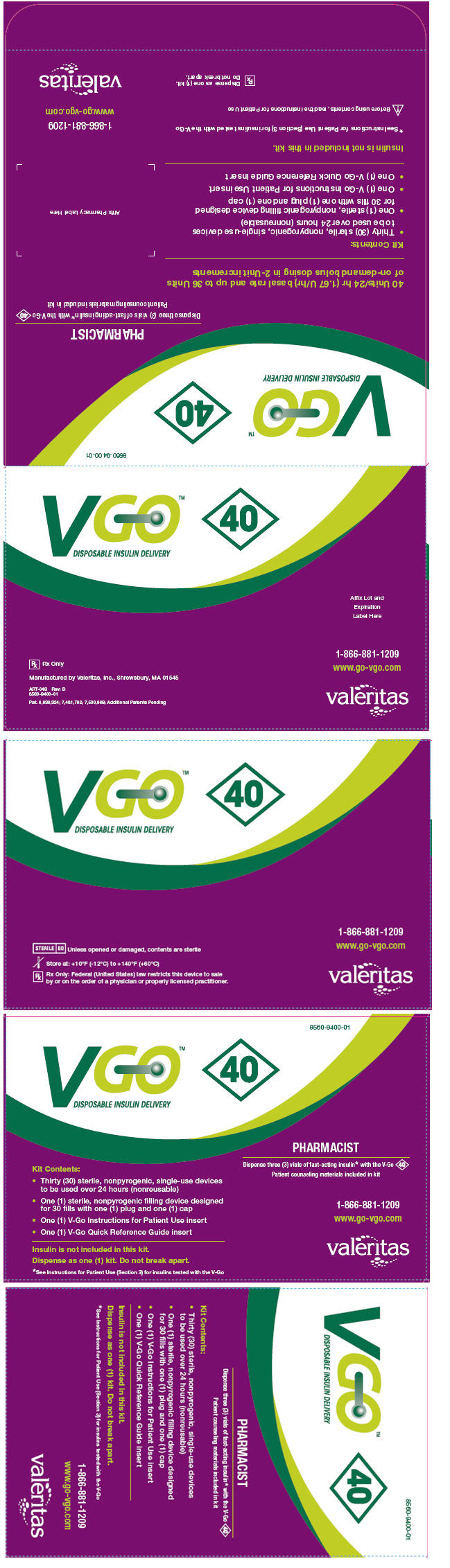 DRUG LABEL: V-GO DISPOSABLE INSULIN DELIVERY DEVICE
NDC: 8560-9400
Manufacturer: Valeritas, Inc
Category: other | Type: PRESCRIPTION MEDICAL DEVICE LABEL
Date: 20130415

VGO
DISPOSABLE INSULIN DELIVERY

Using the V-Go™ Disposable Insulin Delivery Device Instructions for Patient Use

Read the entire manual before operating the V-Go™ Disposable Insulin Delivery Device.

CONTENTS

Section 1 (Part 1): Introduction and V-Go Overview
Healthcare professional prescribing considerations
Valeritas customer care
Liability disclaimer

Section 1 (Part 2): Before You Begin

Section 2 (Part 1): V-Go Operating Instructions
V-Go product overview
EZ Fill product overview
Aseptic technique

Section 2 (Part 2): Filling the V-Go with Insulin Using the EZ Fill
Step 1: Remove the plug from the EZ Fill drawer
Step 2: Place the V-Go into the EZ Fill
Step 3: Place the insulin vial into the EZ Fill insulin vial holder
Step 4: Fill the V-Go with insulin
Step 5: Remove the V-Go from the EZ Fill
Step 6: Store the EZ Fill and unfilled V-Go devices after each day's V-Go filling session
Step 7: Remove an empty vial of insulin from the insulin vial holder and place a new vial of insulin into the insulin vial holder
Step 8: Dispose of the EZ Fill

Section 2 (Part 3): Applying and Using the V-Go
Step 1: Inspect the V-Go before you attach it to your body
Step 2: Wash your hands
Step 3: Select and prepare the infusion site
Step 4: Attach the V-Go
Step 5: Start the 24-hour flow of insulin with the V-Go
Step 6: Bolus dose with the V-Go at mealtimes
Step 7: Monitor V-Go progress
Step 8: Remove the V-Go
Step 9: Dispose of the V-Go

Section 3: V-Go Safety Information
Caution
Indication
Healthcare professional dosing considerations
Warnings
Precautions
Adverse reactions

Section 4: Product Specifications
EZ Fill
V-Go
Delivery accuracy test results

Section 5: V-Go User Assistance Information

Section 6: Troubleshooting/Frequently Asked Questions

Section 7: Glossary and Packaging Symbols

The V-Go Disposable Insulin Delivery Device should be used only by people who have been prescribed the device, and only for intended use.

Terms in bold and italic are explained in the glossary.

SECTION 1 (Part 1): INTRODUCTION AND V-Go™ OVERVIEW

The V-Go provides a continuous subcutaneous insulin infusion over 24 hours. It uses a preset basal rate for between-meal and nighttime insulin. The V-Go provides on-demand bolus dosing to cover glucose intake at meals. The V-Go device is convenient and easy to operate (see Section 3 for indication).

Here is how to use the V-Go:

- Fill the V-Go with insulin using the EZ Fill
- Attach the V-Go to a selected site (skin area)
- Push in the needle button to deliver the preset basal rate
- Wear the V-Go for one (1) 24-hour period
- Bolus dose at meals as prescribed by your doctor or healthcare professional
- At the end of the 24-hour period, retract the needle and remove the V-Go from your body
- Discard the device after use (the V-Go is 100% disposable)
- Repeat these steps for the next 24-hour period using a new V-Go

Healthcare Professional Prescribing Considerations

Dosing considerations

- When selecting a V-Go option, healthcare professionals should refer to their own experience when initiating continuous subcutaneous insulin infusion therapy with a patient. If unfamiliar, the healthcare professional should refer to insulin therapy guidelines from diabetes associations.
- The following should be considered when initially prescribing the V-Go:
  - Understand the total daily dose of insulin your patient is actually taking with their current insulin regimen versus what is being prescribed. Selecting the correct V-Go option may lessen the risk of hypoglycemia (low blood sugar).
  - It is common practice to reduce the total daily insulin dose when starting a patient on continuous subcutaneous insulin infusion therapy and this reduction should be considered when starting a patient on the V-Go.

Other prescribing considerations

- A separate prescription of a U100 fast-acting insulin is required for use with the V-Go (see Section 3 for insulins tested with the V-Go).
  - Two (2) vials of insulin are required for the V-Go 20 option.
  - Three (3) vials of insulin are required for the V-Go 30 and 40 options.

The V-Go comes in 3 options for your insulin needs. Your doctor or healthcare professional has selected the most appropriate V-Go option for you.

The 3 V-Go options are:

- 20 Units/24 hr (0.83 U/hr) basal rate and up to 36 Units of on-demand bolus dosing in 2-Unit increments [36 Units of insulin are available for on-demand bolus dosing in all V-Go options. Bolus doses are delivered in 2-Unit increments. You can only push the bolus delivery button 18 times in every 24-hour period. Each push of the bolus delivery button delivers 2 Units of insulin (1 push = 2 Units).]

- 30 Units/24 hr (1.25 U/hr) basal rate and up to 36 Units of on-demand bolus dosing in 2-Unit increments

- 40 Units/24 hr (1.67 U/hr) basal rate and up to 36 Units of on-demand bolus dosing in 2-Unit increments

IMPORTANT: A separate prescription for insulin is required for use with the V-Go. A U100 fast-acting insulin should be used to fill the V-Go. (See Section 3 for insulins tested with the V-Go.)

- V-Go 20 requires two (2) vials of insulin
- V-Go 30 and 40 require three (3) vials of insulin

IMPORTANT: Let your healthcare professional know how much insulin you actually take each day. Your healthcare professional will help select the correct V-Go option for you.

The correct V-Go option may lessen the risk of hypoglycemia.

IMPORTANT: A V-Go Disposable Insulin Delivery Device that has been properly prescribed and used will deliver your insulin needs. Wear each V-Go for a full 24-hour period, including while you sleep.

IMPORTANT: Do not use other insulin products while on V-Go therapy.

Valeritas Customer Care

If you have any questions about using the V-Go™ or EZ Fill, speak to a Valeritas Customer Care Representative 24/7 at 1-866-881-1209.

If you have a medical emergency while using the V-Go, call 911, your doctor, or go directly to the hospital.

Liability Disclaimer

Valeritas does not give medical advice about insulin therapy. Discuss all medical therapies with your healthcare professional.

SECTION 1 (Part 2): BEFORE YOU BEGIN

Step 1: Remove the EZ Fill from the blister packaging

A. Turn the packaging over so you can read the text.
B. Peel back on the lower right corner.
C. Remove the EZ Fill.

Step 2: Remove the V-Go from the blister packaging

A. Turn the packaging over so you can read the text.
B. Peel back on the lower left corner on one of the V-Go containers.
C. Remove the V-Go. Do not pull on the adhesive tab while removing the V-Go from the container.

NOTE: Only remove one (1) V-Go every 24 hours to fill, apply, and use. Leave the rest in their containers until you are ready to use them.

SECTION 2 (Part 1): V-Go OPERATING INSTRUCTIONS

IMPORTANT: Understanding the button names and locations is important for the successful use of the V-Go and EZ Fill.

V-Go Product Overview

- Button Cover: Covers the needle button. Prevents the needle button from being pushed in. Cover must be removed for V-Go to operate.
- Insulin Port: Location where insulin enters the V-Go through the EZ Fill.
- Bolus Ready Button: A grey button that lies flat on one of the long edges of the V-Go. When activated, it releases the bolus delivery button. This allows for bolus dosing of insulin.

- Bolus Delivery Button: A grey button next to the insulin port on one of the short edges of the V-Go. When pressed after the bolus ready button activates this button, the V-Go delivers a bolus dose of 2 Units of insulin (1 push = 2 Units).
- Viewing Window: Shows a view of the insulin reservoir. A grey indicator in the window demonstrates that insulin is flowing from the device.

- Needle Button: When pressed, it inserts the needle into your skin and begins the flow of insulin into your body.
- Needle Release Button: A wide white button with 3 ridges on one of the long edges of the V-Go. An activated needle release button removes the needle from your body and stops the V-Go from delivering insulin.
- Adhesive Pad and Liner: Once the protective adhesive liner is removed, the adhesive pad affixes the V-Go to your skin.

EZ Fill Product Overview

- Cap: Protects the needle inside the EZ Fill (bottom of insulin vial holder).
- Finger Groove: Opening to allow for easy removal of the insulin vial.
- Insulin Vial Holder: Opening in the EZ Fill where the insulin vial is placed upside down.
- Insulin Supply Window: Shows a view of the insulin remaining in the insulin vial.
- Plunger: When you pull this handle slowly up (about 5 seconds) and then push it down (about 25 seconds), insulin transfers from the vial into the V-Go™.
- Grip: The left thumb occupies this groove throughout most of the filling process.
- Drawer: The V-Go is placed in this drawer for filling. The plug sits in the drawer when the EZ Fill is not in use.
- Ribbed Drawer Handle: A grooved piece at the bottom end of the EZ Fill that helps with opening and closing the drawer.
- Plug: When placed in the drawer, the plug protects the EZ Fill components between each fill.

Aseptic Technique

Aseptic technique helps keep the V-Go and the EZ Fill devices clean during preparation, filling, and application. Following this technique requires hand-washing and wiping the application site with an alcohol swab. It may involve wiping the V-Go device with an alcohol swab if the device comes into contact with anything else.

Use aseptic technique when you are preparing, filling, and attaching a new V-Go.

1. Inserting a needle into your skin creates an opening where germs can enter your body. This could cause an infection at the infusion site. Always use aseptic technique. The V-Go, EZ Fill, and other supplies come to you sterilized. To keep them that way, follow these precautions:
  a. Always wash your hands thoroughly before preparing, filling, and attaching the V-Go.
  b. The infusion needle is sterile and protected within the V-Go. Do not touch the underside of the V-Go after you remove it from the sterile blister packaging. If you place the V-Go on a surface, do not let the underside touch that surface. Gently lay the V-Go on the front side of the device.
2. If the underside of the V-Go touches something, you must wipe the underside with an alcohol swab.
3. Do not touch the circular opening on the top of the EZ Fill plug. If you place the plug on a surface, do not let the circular opening touch that surface. If the circular opening touches something, you must wipe the circular opening with an alcohol swab.
4. Wipe the infusion site of your skin with an alcohol swab. Let the alcohol dry before you attach the V-Go. Do not touch this site again before putting the V-Go on your skin.

SECTION 2 (Part 2): FILLING THE V-Go™ WITH INSULIN USING THE EZ FILL

IMPORTANT:

The EZ Fill is intended to fill one (1) V-Go each day.

Use the EZ Fill to fill 30 V-Go devices, one (1) V-Go each day. Then discard the EZ Fill after 30 fills.

A new EZ Fill will be included in each month’s supply of V-Go devices.

Do not fill and store V-Go devices ahead of time. That may result in the loss of insulin effectiveness.

Remove the EZ Fill from the refrigerator, allowing the insulin to reach room temperature (about 20 minutes) before filling the V-Go.

Step 1: Remove the plug from the EZ Fill drawer

NOTE: On day 1 when you remove the EZ Fill from the packaging, the plug will be separate from the EZ Fill; therefore, you can skip Step 1.

A. Place your thumb over the plug tab and your forefinger underneath the ribbed drawer handle. Pull the drawer out until it stops. The plug will pop up from the drawer.
B. Lift the plug out of the EZ Fill using your thumb and forefinger. Set the plug aside. You will replace the plug into the EZ Fill after you fill the V-Go with insulin.

IMPORTANT: People should not touch the circular opening on the top of the plug. Touching the circular opening may compromise the sterility of the EZ Fill.

Step 2: Place the V-Go into the EZ Fill

A. Hold the EZ Fill so that the plunger is on the top right side of the EZ Fill.
B. With your other hand, place the V-Go into the EZ Fill drawer upside down. Place the adhesive side facing up with the plastic tab toward the bottom of the EZ Fill. The button cover should be facing down into the drawer and toward the top of the EZ Fill.

C. Slide the V-Go up into the EZ Fill drawer. Press the V-Go flat with the top of the drawer. Hold the V-Go down with your thumb.
  - Make sure that the adhesive backing on the V-Go fits inside the drawer.

D. Push the drawer all the way closed.

IMPORTANT: Shut the EZ Fill drawer only when the V-Go is completely inside the drawer. The drawer is shut when it cannot be pushed any further forward or in.

Step 3: Place the insulin vial into the EZ Fill insulin vial holder

NOTE: Before placing a new vial into the EZ Fill, check to make sure the insulin vial is not expired and that it will not expire during the time period that the vial will be used in the EZ Fill.

A. Remove the protective cap from the insulin vial. Wipe the top with an alcohol swab.

B. Pull the EZ Fill cap out of the insulin vial holder and discard.

C. Turn the insulin vial upside down so the top of the vial faces downward.
D. Place the insulin vial into the EZ Fill. Push the vial firmly straight down into the insulin vial holder until you feel it attach and you cannot push it further.
E. Check the insulin supply window to make sure there is enough insulin to fill the V-Go™.

Step 4: Fill the V-Go with insulin

A. Hold the EZ Fill upright over a counter or table by placing your thumb across the grip. The grip is just below the insulin vial holder and the plunger. Use the rest of your hand to support the back of the EZ Fill.
  - Do not block light from the back of the EZ Fill. Light from the back will help you see the viewing window.

NOTE: Keep the EZ Fill in a vertical, fully upright position during filling.

Keep the viewing window at eye level. Direct the backside of the EZ Fill toward a brightly lit area when you fill the V-Go. This makes it easier to see the flow of insulin. Seeing the flow of insulin helps you fill the V-Go properly and completely.

B. Slowly pull the plunger up to its full upright position with your free hand and wait 5 seconds.

IMPORTANT: Make sure you slowly pull the plunger up as far as it can go.

C. Make sure the viewing window is at eye level so you can watch the V-Go fill with insulin.

D. Slowly and steadily push the plunger down over a minimum of 25 seconds to fill the V-Go™ with insulin.
  - The V-Go should be filled with insulin in a continuous flow of droplets, not in a solid, steady stream. Make sure you don't fill the V-Go with a steady stream of insulin. If you push too fast or too hard the insulin will become foamy. Foamy insulin may lead to an incomplete fill. If the insulin turns foamy, push the plunger more slowly.

IMPORTANT: Watch the insulin fill the V-Go to make sure you get a complete fill.

E. Push the plunger until it is all the way down.
  - When the position of the plunger is all the way down, the V-Go should be full.

IMPORTANT: Make sure the V-Go fills with insulin in a continuous flow of droplets, not in a solid, steady stream. Make sure the insulin is not foamy. Foam will not damage the V-Go or the insulin, but may lead to an incomplete fill of the V-Go.

Count to about 25 seconds when you push the plunger down to make sure the V-Go is filled with insulin.

F. Check that the V-Go is filled properly. Ideally you should see only fluid and no air space. You may see tiny air bubbles smaller than a grain of rice.
  - If the V-Go is not filled fully, check to see if you still have insulin in your vial.
    - If you do not, replace vial (Step 3) and repeat Step 4A to 4F.
    - If you do, repeat Step 4A to 4F.

IMPORTANT: Make sure the V-Go is completely full of insulin before removing from the EZ Fill. If the V-Go does not appear completely full, repeat Step 4A to 4F.

Step 5: Remove the V-Go from the EZ Fill

A. Hold the EZ Fill in a sideways position.
B. Pull the EZ Fill ribbed drawer handle all the way out. Pull until the V-Go pops up from the drawer.

C. Remove the filled V-Go from the EZ Fill by lifting it up with your thumb and forefinger.
  - Leave the plunger in the down position.

REMINDER: Fill only one (1) V-Go each day. Fill the V-Go on the day you use it, and attach the V-Go to your skin immediately after filling it with insulin.

Step 6: Store the EZ Fill and unfilled V-Go™ devices after each day's V-Go filling session

A. Place the plug back into the EZ Fill. Follow the directions for filling Step 2A to 2D. This time use the plug and not a V-Go.

NOTE: Do not remove the insulin vial from the EZ Fill. The insulin vial should be removed only when the vial is empty.

IMPORTANT: To make sure the EZ Fill remains sterile:

- Replace the plug after each fill.
- Wipe the circular opening on top of the plug with an alcohol swab before placing the plug back into the EZ Fill.

B. Store the EZ Fill with the insulin vial and plug attached in a clean, dry area of the refrigerator between each fill. Store unfilled, unused V-Go devices in a dry, safe place until your next fill. Please refer to Section 4 for additional storage information.

Additional Steps

Step 7: Remove an empty vial of insulin from the insulin vial holder and place a new vial of insulin into the insulin vial holder

NOTE: Before placing a new vial into the EZ Fill, check to make sure the insulin vial is not expired and that it will not expire during the time period that the vial will be used in the EZ Fill.

A. Grasp the vial along the finger and thumb grooves. Pull up the vial to remove it from the EZ Fill.

B. To place a new vial of insulin into the EZ Fill, follow filling Step 3A to 3E.

Step 8: Dispose of the EZ Fill

A. After the 30-fill use period, discard the EZ Fill, with the insulin vial attached, according to local disposal requirements. The insulin vial should be discarded even if there is insulin remaining in the vial.

IMPORTANT: The EZ Fill is only intended to fill a 30-day supply of V-Go devices (1 V-Go per day). A new EZ Fill will be provided with each monthly prescription of the V-Go.

Do not use the same EZ Fill for more than 30 fills.

SECTION 2 (Part 3): APPLYING AND USING THE V-Go™

Step 1: Inspect the V-Go before you attach it to your body

A. Look at the entire viewing window to make sure that the V-Go has been filled completely with insulin. You should see only fluid and no air space.
B. Rotate the V-Go and look in the viewing window. The viewing window will show you if there are any large air bubbles.

IMPORTANT: If you see air bubbles larger than a grain of rice, the V-Go may not be filled completely. Repeat Step 4A to 4F in Section 2 (Part 2) to ensure a complete fill.

Having a few small bubbles is normal and harmless.

As discussed in Section 2 (Part 2), you should slowly and steadily push the plunger down for about 25 seconds to reduce air bubbles as you fill the V-Go.

C. When the insulin is full in the viewing window, you are ready to attach the V-Go to your body.

IMPORTANT: To receive your total 24-hour dose of insulin, always start with a V-Go that has been completely filled with insulin.

Do not attach a partially filled or empty V-Go to your body. If the V-Go is not filled completely with insulin, repeat Step 4A to 4F in Section 2 (Part 2).

Step 2: Wash your hands

Always wash your hands thoroughly before preparing the V-Go for use. Use aseptic technique when you are preparing and applying a new V-Go. See the end of Section 2 (Part 1) for a description of aseptic technique.

Step 3: Select and prepare the infusion site

IMPORTANT: The place on your body where you attach the V-Go is important for the success of your therapy. Choose a location that remains flat when you are sitting down, standing up, or lying down. Discuss the best location for you with your doctor or healthcare professional.

A. The V-Go can be worn any place that insulin can be injected or infused. Insulin is injected or infused into the subcutaneous tissue.
  - You may wish to attach the V-Go:
    - On the abdomen. The abdomen has ample flat surface area, and is an accessible and comfortable location. Insulin absorption is fast, predictable, and less affected by exercise when administered through the abdomen.
      - If the V-Go is worn on the abdomen, keep it horizontal above the belt line.
    - On the backside of the arm, not on the muscle.
      - If the V-Go is worn on the backside of the arm, keep it in the up and down direction. Make sure you can see the grey indicator in the viewing window directly by rotating your arm, or indirectly through the use of a mirror. Attach the V-Go in the up and down position as your arm hangs down.
B. When choosing the location for the V-Go™, consider the following:
  - Make sure you are able to view the grey indicator in the viewing window, either directly or indirectly through the use of a mirror.
  - That you can comfortably reach the V-Go and all of the buttons, for easy operation and removal.
  - That you apply the V-Go to a flat area of skin, not on a fold of the skin, muscle, or bone.
  - That the site is flat when you are in any of the following positions: sitting down, standing up, or lying down.

C. When choosing the location for the V-Go, avoid the following:
  - The belt line or waistline, or other areas where clothing may rub or constrict.
  - Areas with excessive hair. You may shave the area to help the V-Go attach to your skin.
  - Areas that are curved or rigid due to muscle or bone.
  - Areas within a 1-inch circle around the belly button or surgical scars.
  - Skin that is tender, bruised, red, or hard or has any skin disease or infection.

NOTE: If you have sensitive skin or your skin becomes irritated, ask your doctor or healthcare professional about skin barrier products.

NOTE: Change the location of the V-Go slightly every 24 hours. Needle insertion sites should be at least 1 inch away from the last site.

This may mean moving it from the right to the left side of the abdomen. It does not require attaching the V-Go on the abdomen one day then on the arm the next.

D. Clean the area where you will attach the V-Go with an alcohol swab.
  - The alcohol swab will remove all lotions and oils. Let the area dry. This helps the adhesive stick properly to the skin.
  - Practice aseptic technique as described in Section 2 (Part 1).

Step 4: Attach the V-Go

Actions in this step describe how to attach the V-Go to your abdomen. As noted in Section 2 (Part 3) Step 3, there are a couple of places you can attach the V-Go.

A. Practice placing the V-Go before you actually remove the protective liner. Practice helps you to make sure you can reach and operate the bolus ready button, bolus delivery button, needle button, and needle release button.
  - To practice with your right hand, hold your thumb on the needle release button, your index finger near but not on the bolus delivery button, and middle finger near the bolus ready button.
  - Hold the V-Go on the selected body site to make sure that you can reach all necessary buttons when you wear the V-Go.

Now you are ready to attach the V-Go.

IMPORTANT: Be careful not to press any buttons when you practice attaching the V-Go.

B. Remove the button cover.
  1. Hold the V-Go™ with one hand and pull the button cover with the other hand. Pull the button cover in a quick, straight direction up and away from the V-Go.

2. Check to see if the cover pin came off with the button cover.
  - If the cover pin is not attached and has remained inside the V-Go, try to remove the pin manually; otherwise discard this V-Go and start over with a new V-Go.

IMPORTANT: If you bend the button cover backwards, as you would a soda pop can top, you could damage the V-Go.

C. Lift the adhesive tab and completely peel off the adhesive liner from the bottom of the V-Go. Removing the liner exposes the adhesive.
  1. Do not touch the adhesive surface. Touching the adhesive surface can reduce the strength of the adhesive.
  2. Keep the adhesive pad intact and clean before you place it on the infusion site.

D. Without touching the adhesive pad, press the V-Go against the skin at the cleaned needle infusion site.
E. Hold the V-Go in place for 5-10 seconds. Run your finger around the entire edge of the adhesive pad to make sure it is attached to your body. Do not accidentally press any of the buttons.

NOTE: When you apply the V-Go to the abdomen, attach the V-Go horizontally at a slight downward angle. This allows any tiny air bubbles to travel away from the needle.

Step 5: Start the 24-hour flow of insulin with the V-Go

Press down on the raised bump of the needle button with one firm quick motion. Needle button needs to be pressed completely into the V-Go until you hear a click or button locks in place. This begins the flow of insulin. The V-Go delivers a continuous preset basal rate of insulin over 24 hours.

NOTE: Grasp the side of the V-Go as you press the raised bump of the needle button to keep the V-Go in place.

Be careful not to press any other buttons during this process.

IMPORTANT: Needle button must lock in place to begin the flow of insulin.

IMPORTANT: Avoid exposing the V-Go™ to direct sunlight. Avoid extremely hot temperatures. Remove the V-Go prior to hot tub, whirlpool, or sauna use and replace with a new filled V-Go afterward.

IMPORTANT: If the needle button does not fully depress or does not remain in the down position, the V-Go cannot function. You will not receive the preset basal rate of insulin. Do not use the V-Go if the needle button does not stay down. Remove and discard that V-Go. Start over with a new V-Go.

Once the needle button is pushed down and locks into place, insulin is now flowing into your body. The needle within the V-Go remains in your body for the entire 24-hour use of the V-Go. The V-Go design helps to minimize discomfort.

IMPORTANT: Stop all your previous insulin injections and do not use any other insulin in conjunction with the V-Go Disposable Insulin Delivery Device.

NOTE: You should check the area around the V-Go at regular intervals for redness, irritation, and inflammation.

Step 6: Bolus dose with the V-Go at mealtimes

Your doctor or healthcare professional should have instructed you on how and when to use the V-Go and how many bolus doses to administer at mealtimes. Consult your doctor or healthcare professional if you have questions regarding your specific bolus dosing needs.

IMPORTANT: Each V-Go has a total of 36 Units of insulin available for on-demand bolus dosing per 24-hour period. The 36 Units of insulin can only be delivered in 2-Unit increments (1 push = 2 Units). You can only push the bolus delivery button 18 times in every 24-hour period. After 18 uses, the bolus delivery button will pop out and lock, preventing further bolus doses. Plan your day so that you have enough insulin for each meal.

A. To administer 2 Units of insulin at mealtime:
  1. Slide your finger with pressure to locate and press the bolus ready button on the long edge of the V-Go.
    - The bolus delivery button located at the end of the V-Go will pop out. You will hear a click.

2. Push the bolus delivery button all the way into the V-Go until it stops. You will hear another click.
  - You have just delivered 2 Units of insulin (1 push = 2 Units).

IMPORTANT: Do not touch the needle release button (button with ridges) while giving yourself bolus doses. This may cause you to retract the needle before the end of its 24-hour use and stop the delivery of insulin to your body. If this occurs and the needle button pops out, remove the V-Go and replace it with a new one.

B. Repeat Step 6A until you reach the number of bolus doses prescribed by your doctor or healthcare professional for that specified time.

NOTE: Each push of the bolus delivery button delivers 2 Units of insulin (1 push = 2 Units).

IMPORTANT: If you do not know the number of insulin units you have just delivered or if you lose count, STOP bolus dosing, monitor your blood glucose, and follow the plan agreed upon with your doctor or healthcare professional. If you have not agreed upon a plan already, consult your doctor or healthcare professional for guidance.

IMPORTANT: If the bolus ready button or bolus delivery button does not press in or does not click when pressed, you may have used all of the available bolus doses. If you require additional bolus doses, do not continue to use this V-Go™. Replace it with a new filled V-Go.

Step 7: Monitor V-Go progress

A. While wearing the V-Go, you should check your blood glucose at regular intervals to make sure the V-Go is working properly. Refer to Section 3 for recommendations on blood glucose monitoring.
B. You can also check the movement of the grey indicator in the viewing window to make sure the V-Go is working properly. After several hours, you should see a slight change in the location of the grey indicator as it moves toward the needle button.
  - The exact location of the grey indicator will vary based on the number of bolus doses you have used.

IMPORTANT: The indicator moves very slowly over the 24-hour period. It will take time to notice the change in the indicator location.

Monitoring the V-Go progress is important to make sure the V-Go is delivering insulin. If the indicator does not appear to be moving after several hours of wearing the V-Go, consider checking your blood glucose levels. If your levels are abnormally high after normal V-Go use as prescribed by your doctor or healthcare professional, you should remove the V-Go and replace it with a new one.

Step 8: Remove the V-Go

IMPORTANT: After 24 hours of use it is time to replace the current V-Go with a new filled V-Go. Remember to fill the V-Go with insulin using the EZ Fill, and attach the V-Go to your skin immediately after filling.

The V-Go is meant to be worn for 24 hours only. Establishing a daily routine will help remind you to change the V-Go every 24 hours.

A. Start by filling a new V-Go with insulin. Follow previous instructions in Section 2 (Part 2) Steps 1 to 6.
  - Make sure the V-Go is completely filled with insulin before you attach.
B. Set the new filled V-Go aside until you remove the used V-Go from your skin.

NOTE: Do not block the needle button with your finger or any part of your hand or clothing while releasing the needle via the needle release button.

C. To remove the used V-Go™, place thumb on the ridged section of the needle release button. Slide the needle release button along the side of the V-Go. In a continuous motion, press the needle release button directly into the V-Go until you hear a click. This motion retracts the needle.

D. At this point the needle button will pop out automatically.

E. To remove the V-Go from your skin, run a finger under an edge of the adhesive pad.

F. Press lightly on the skin adjacent to the V-Go with one hand and peel the V-Go away from your skin with the other hand.

NOTE: After you remove the V-Go, the adhesive may leave behind a sticky residue. Use warm soapy water and roll your finger around the attachment site. This motion will remove the sticky adhesive residue.

You could use a medical adhesive remover instead. Ask your doctor or healthcare professional to recommend an adhesive remover.

Step 9: Dispose of the V-Go

Discard the used V-Go according to local disposal requirements.

NOTE: When used as directed, the V-Go needle is never exposed. It comes out only when the device is attached to the skin. After use, the needle is retracted back into the V-Go and locked. Once retracted, the V-Go needle is completely contained/covered.

Check to make sure the needle is retracted. If it is not, repeat Step 8C prior to disposal of the V-Go.

SECTION 3: V-Go™ SAFETY INFORMATION

The V-Go is a safe and reliable device. As with many medical devices, you must be aware of safety-related issues to make sure that you are using the V-Go correctly. Always consult with your doctor or healthcare professional if you have any questions regarding the functions and operation of the V-Go.

Caution

Federal (United States) law restricts this device to sale by or on the order of a physician or properly licensed practitioner (prescription only).

Indication

V-Go 20:
The V-Go Disposable Insulin Delivery Device is indicated for continuous subcutaneous infusion of 20 Units of insulin in one 24-hour time period (0.83 U/hr) and on-demand bolus dosing in 2-Unit increments (up to 36 Units per one 24-hour time period) in adult patients requiring insulin.

V-Go 30:
The V-Go Disposable Insulin Delivery Device is indicated for continuous subcutaneous infusion of 30 Units of insulin in one 24-hour time period (1.25 U/hr) and on-demand bolus dosing in 2-Unit increments (up to 36 Units per one 24-hour time period) in adult patients requiring insulin.

V-Go 40:
The V-Go Disposable Insulin Delivery Device is indicated for continuous subcutaneous infusion of 40 Units of insulin in one 24-hour time period (1.67 U/hr) and on-demand bolus dosing in 2-Unit increments (up to 36 Units per one 24-hour time period) in adult patients requiring insulin.

A U100 fast-acting insulin should be used with the V-Go. Humalog® (insulin lispro, rDNA origin) and NovoLog® (insulin aspart, rDNA origin) have been tested by Valeritas, Inc. and found to be safe for use in the V-Go Disposable Insulin Delivery Device.

Before using different insulin with the V-Go, you should check the insulin label to make sure it can be used with this device.

Healthcare Professional Dosing Considerations

When selecting a V-Go option, healthcare professionals should refer to their own experience when initiating continuous subcutaneous insulin infusion therapy with a patient. If unfamiliar, the healthcare professional should refer to insulin therapy guidelines from diabetes associations.

The following should be considered when initially prescribing the V-Go:

- Understand the total daily dose of insulin your patient is actually taking with their current insulin regimen versus what is being prescribed. Selecting the correct V-Go option may lessen the risk of hypoglycemia.
- It is common practice to reduce the total daily insulin dose when starting a patient on continuous subcutaneous insulin infusion therapy and this reduction should be considered when starting a patient on the V-Go.

Warnings

Insulin requirements

If you have to make regular adjustments or modifications to your basal rate during a 24-hour period, or if the amount of insulin used at meals requires adjustments of less than 2-Unit increments, use of the V-Go may result in hypoglycemia.

The following conditions may occur during insulin therapy with the V-Go.

- Hypoglycemia:
  - Intensive management of diabetes with too much insulin has been associated with an increase in the incidence of hypoglycemia (low blood sugar).
- Hyperglycemia and diabetic ketoacidosis (DKA):
  - Any insulin delivery interruption may result in hyperglycemia (high blood sugar) or the onset of diabetic ketoacidosis.

If you have a medical emergency while using the V-Go, call 911, your doctor, or go directly to the hospital.

Precautions

General

The following are a number of general precautions you should consider when using the V-Go™ Disposable Insulin Delivery Device.

The V-Go is magnetic resonance (MR) unsafe.

You should remove the V-Go before having an X-ray, MRI, or CT scan (or any similar test or procedure). Replace with a new V-Go after the test or procedure is completed.

You should monitor your blood glucose levels based on your doctor's or healthcare professional's recommendation. American Diabetes Association guidelines suggest that patients test blood glucose 3 or more times daily.

You should act quickly to respond to abnormal blood sugar levels.

- Notify your doctor or healthcare professional of any serious hypoglycemia or hyperglycemia. Tell your doctor or healthcare professional of any increased frequency in abnormally high or low blood glucose test results.

You should create a plan with your doctor or healthcare professional in case a problem occurs when you are unable to reach him or her for advice.

You should create a plan with your doctor or healthcare professional on how to manage your bolus (mealtime) dosing using the V-Go, including what to do if you lose count while bolus dosing or if you forget to take a bolus dose.

You should carry an emergency kit of insulin supplies, if instructed by your doctor or healthcare professional, in case you develop a problem with the V-Go that stops your insulin delivery. Tell a family member or friend where you keep your emergency kit items.

- You should speak with your doctor or healthcare professional regarding what to have in the emergency kit, which often includes the following items:
  - Fast-acting glucose tablets
  - Blood glucose and urine ketone monitoring supplies
  - Back-up insulin, insulin syringe, and needles with directions from your doctor or healthcare professional regarding how much insulin to take
  - Dressing and adhesive

You should avoid exposing the V-Go to direct sunlight.

You should avoid exposure to extremely hot temperatures. Remove the V-Go prior to hot tub, whirlpool, or sauna use and replace with a new filled V-Go afterward.

You should check that the V-Go is securely in place during and after periods of increased physical activity. Check that the V-Go is securely in place if it has been exposed to water or gone under water to the depth of 3 feet, 3 inches (1 meter). The V-Go can go under water and will continue to work safely.

You should follow these precautions to help prevent problems with the V-Go placement:

1. Never use insulin that appears cloudy. Cloudy insulin may be inactive. Do not use cloudy insulin with the V-Go.
2. Do not expose the insulin to extreme changes in temperature. Check the insulin package insert for temperature variation.
3. Practice aseptic technique when preparing, filling, and attaching the V-Go.
4. Check the adhesive site for redness, irritation, and inflammation when you remove a used V-Go and before you attach a new V-Go.
5. Change the application site each time you change the V-Go. See Section 2 (Part 3) Step 3. Changing the site will ensure proper absorption of insulin. The new site should be at least 1 inch away from the previous site.
6. Do not apply the V-Go to a site that has excess hair or is irritated, infected, or unhealthy for any reason. Consult with your doctor or healthcare professional about how to prepare and maintain these sites.
7. Avoid attaching the V-Go to sites that may interfere with your clothing, accessories, or car seatbelts.
8. Do not attach the V-Go to sites with rigorous movement and stretching due to exercise or job-related activities.

Hypoglycemia

Low blood sugar is the most common side effect associated with any insulin, including the insulin delivered using the V-Go™. Symptoms of low blood sugar may vary and can happen suddenly.

To help prevent hypoglycemic episodes, follow these precautionary steps:

1. Know the symptoms of hypoglycemia. Do not ignore these symptoms, no matter how mild they may be.
2. Always carry a fast-acting sugar replacement (such as candy, juice, or glucose tablets) in the event of a hypoglycemic episode.
3. The V-Go delivery rate can vary by up to +/- 10% from device to device. Even though the chance of this happening is remote, you should monitor your glucose level at least 3 times per day or as recommended by your doctor. Your doctor or healthcare professional may recommend specific times for you to check your blood glucose.
4. Check your blood glucose before driving or operating heavy machinery. Appropriate blood glucose levels are required to maintain alertness.

IMPORTANT: If your glucose level falls below 70 mg/dL, you may be hypoglycemic (low blood sugar) and you should take immediate action to raise your blood glucose level. This may be done by taking glucose tablets, eating candy, drinking juice, or doing as your doctor or healthcare professional instructs. You should retest your blood glucose after 15 minutes and if it is still below 70 mg/dL continue to take steps to increase your blood glucose level until it reaches your normal level.

Consult with your doctor or healthcare professional to understand how to best recognize and manage low blood glucose.

Hyperglycemia and Diabetic Ketoacidosis (DKA)

To help prevent serious hyperglycemia (high blood sugar) and the possibility of diabetic ketoacidosis (DKA), follow these precautions:

1. Check your blood glucose frequently based on your doctor’s or healthcare professional's recommendation. Your doctor or healthcare professional may recommend specific times for you to check your blood glucose.

IMPORTANT: Nausea and vomiting are often the first signs of DKA. To avoid DKA, be prepared and act quickly. Don’t assume your blood glucose is high because you are under stress, have the flu, or miscalculated your last meal bolus.

2. Be sure you know when to test for ketones and when your doctor or healthcare professional expects you to call with results.
3. Know your blood glucose target ranges and when your doctor or healthcare professional expects you to report trouble. When your blood glucose is high, be prepared to administer insulin. If you suspect that the V-Go is not delivering insulin, refer to the Troubleshooting section of this manual on page 41.
4. Keep yourself well hydrated, especially during illness or exercise.
5. Do not treat DKA yourself. If you suspect DKA, contact your doctor or healthcare professional.

Adverse Reactions

Site Infection/Abscesses

Infections at the infusion site may occur. Proper site preparation and frequent site rotation (refer to Section 2 (Part 3) Step 3A to 3D) can minimize infections. Remove the V-Go immediately if the area around the V-Go becomes sore, red, or swollen. Apply a new V-Go to a new, clean site away from the suspected infected area. Do not discontinue therapy without the advice of your doctor or healthcare professional.

Skin Irritation

A more common problem than infection is skin irritation. Skin may become irritated by the adhesive pad on the V-Go or by the way the V-Go is positioned on your skin. Skin irritation can occur but does not lead to any further clinical complication.

NOTE: If you have sensitive skin or your skin becomes irritated, ask your doctor or healthcare professional about skin barrier products.

SECTION 4: PRODUCT SPECIFICATIONS

EZ Fill
Storage Conditions – Unused Device Only | -4°F (-20°C) to +140°F (+60°C) 20% to 90% relative humidity
Operating Conditions | +40°F (+5°C) to +99°F (+37°C) 20% to 90% relative humidity Warm to room temperature to optimize fill quality
Insulin | Each time before placing a new vial into the EZ Fill, check to make sure the insulin vial is not expired and that it will not expire during the time period that the vial will be used in the EZ Fill
Duration of Use | 30 fills
Disposal | Local disposal requirements

V-Go™
Basal Delivery, Continuous Subcutaneous | 20 Units/24 hr (0.83 U/hr) 30 Units/24 hr (1.25 U/hr) 40 Units/24 hr (1.67 U/hr)
Bolus Delivery, On-Demand | Each push of the bolus delivery button provides 2 Units Each V-Go contains 18 uses for a maximum of 36 Units per V-Go
V-Go Minimum Capacity Reservoir | 0.56 mL V-Go 20 0.66 mL V-Go 30 0.76 mL V-Go 40
V-Go Size | 2.4 x 1.3 x 0.5 inches (6.1 cm x 3.3 cm x 1.3 cm)
V-Go Weight | 0.7 to 1.8 ounces (20 to 50 grams)
Storage Conditions – Device Only | +10°F (-12°C) to +140°F (+60°C) 20% to 90% relative humidity Avoid prolonged exposure to the extremes of the storage temperature range
Storage Conditions – Filled with Humalog® | The V-Go may be filled with Humalog for up to 24 hours prior to use if refrigerated or if left at room temperature
Storage Conditions – Filled with NovoLog® | The V-Go may be filled with NovoLog for up to 5 days prior to use if refrigerated The V-Go may be filled with NovoLog for up to 3 days prior to use if left at room temperature
Operating Conditions | +40°F (+5°C) to +99°F (+37°C) 20% to 90% relative humidity Do not expose the V-Go to temperatures over 99°F for prolonged periods of time (beyond 14 hours) as this may lead to degradation of the insulin (check the insulin manufacturer's instructions for use for temperature details) and may cause the V-Go to run at a basal rate slightly greater than the specified range
Operating Atmospheric Pressure | 697 hPa to 1,013 hPa (Equivalent to altitudes up to 10,000 feet [3,048 meters])
Duration of Use | 24 hr
Bolus Delivery Accuracy (For all 3 V-Go options) | +/-10%
Basal Delivery Accuracy (For all 3 V-Go options) | +/-10%
V-Go Power Source | Mechanical
Enclosure Protection | Protects against the effects of submersion at depths up to 3 feet, 3 inches (1 meter) for 24 hours. (IPX8)
Needle | 4.6-mm, 30-gauge needle with sharps injury prevention features and floating needle technology
Disposal | Local disposal requirements

Delivery Accuracy Test Results

The following graphs show the basal flow rate accuracy for all 3 V-Go™ options (20/30/40) for the given time periods.

The bolus accuracy is +/-10% for all 3 V-Go options.

Flow Rate Start-up Graphs

Flow Rate Test Period Graphs

SECTION 5: V-Go™ USER ASSISTANCE INFORMATION

Valeritas Customer Care

You may have questions or concerns when you use a new product. Please contact us for advice or assistance. A trained staff member will help you with any questions on how to fill, apply, or use the V-Go.

For specific treatment questions, information on insulin, or medical advice, call your doctor or healthcare professional.

If you have any questions regarding the operation of the V-Go or EZ Fill, speak to a Valeritas Customer Care Representative 24/7 at 1-866-881-1209.

Customers can visit the Valeritas website (www.valeritas.com) for additional information about disposable insulin delivery with the V-Go.

If you have a medical emergency while using the V-Go, call 911, your doctor, or go directly to the hospital.

SECTION 6: TROUBLESHOOTING/FREQUENTLY ASKED QUESTIONS

How do I know how much insulin to put into the V-Go?

You always fill the V-Go completely. The V-Go comes in 3 options and your doctor or healthcare professional will select the option you need.

Why does insulin leak from the EZ Fill?

Check to make sure a V-Go is placed in the EZ Fill before a new insulin vial is placed into the insulin vial holder. This may reduce any insulin leak that can happen when extra pressure is built up in the vial upon initial puncture. Also, make sure the plug is properly inserted into the EZ Fill between fills.

It looks like the V-Go has not filled completely.

There are 5 reasons the V-Go may not fill completely:

1. The insulin vial is not completely pushed down into the insulin vial holder.
  - If this is the case, push the vial firmly straight down into the insulin vial holder until you feel it attach and cannot push it further.
2. You have run out of insulin in your vial. You have to switch vials before you can fill the rest of the V-Go.
  - If this is the case, keep the V-Go in the EZ Fill drawer. Remove the insulin vial from the EZ Fill insulin vial holder, replace with a new vial, and refill the V-Go.
3. You did not completely pull the plunger to its full upright position.
  - If this is the case, slowly pull the plunger up completely and repeat the filling process for the V-Go.
4. You have pushed down the plunger too quickly, which turned the insulin foamy. The foam could become an air bubble larger than a grain of rice.
  - If this is the case, the EZ Fill cannot correct this error at this time. Set the V-Go aside for use on the next day and start over with a new V-Go.
    - The V-Go with the foamy insulin should be stored with the insulin port up. Before using this V-Go, refill it completely with insulin. See Section 2 (Part 2) Step 4A to 4F. Refer to the V-Go storage conditions in Section 4.
5. The EZ Fill drawer may not be completely closed.
  - If this is the case, check again to ensure the drawer is pushed all the way closed.

In any of these situations follow Step 4A to 4F to make sure you have a complete fill.

I am looking in the viewing window while pushing the plunger down, but I don’t see the V-Go™ filling.

There are 2 reasons you may not see any insulin fill the V-Go.

1. You have run out of insulin in your vial. You have to switch vials before you can fill the rest of the V-Go.
  - If this is the case, keep the V-Go in the EZ Fill drawer. Remove the insulin vial from the EZ Fill insulin vial holder, replace with a new vial, and refill the V-Go.
2. You did not completely shut the EZ Fill drawer.
  - Grip the ribbed drawer handle and push the drawer completely into the EZ Fill. The ribbed drawer handle should not stick out past the bottom of the EZ Fill.

If there is insulin in the vial and the drawer is completely shut, try to fill a new V-Go. If you are unable to fill a new V-Go, speak to a Valeritas Customer Care Representative at 1-866-881-1209.

There are bubbles in the insulin vial.

The most common reason for bubbles in the insulin vial is filling more than 1 V-Go at a time. The EZ Fill is designed to fill only 1 V-Go per day.

It is harder to push the plunger when it gets closer to the downward position.

This is normal. When the V-Go is full or close to full, you should expect to push a little harder. You may need a little extra pressure to push the plunger completely down.

What happens if I do not pull the plunger completely up when I fill the V-Go?

If the plunger is pulled only part of the way up during the fill process, you will get only a partial fill of the V-Go. You will see air bubbles in the V-Go viewing window. Keep the V-Go in the EZ Fill drawer and slowly pull the plunger up completely again. Make sure the plunger is completely up. Slowly and steadily push the plunger back down over about 25 seconds until it is in the complete down position.

I tried to pull the plunger up and it snapped back down. What should I do?

Try slowly pulling the plunger up again, but count the full 5 seconds before releasing or reversing the direction of the plunger. The plunger snaps back down if you try to pull the plunger up and release it in less than 5 seconds.

After I place the V-Go into the EZ Fill drawer, what happens if the plunger is already in the up position?

You can still fill the V-Go. Hold the EZ Fill upwards and slowly and steadily push the plunger down over about 25 seconds until it is in the complete down position. As you push the plunger down, check to make sure insulin enters the V-Go. Repeat the plunger cycle if no insulin entered the V-Go or if additional insulin is required to fill the V-Go. See Section 2 (Part 2) Step 4A to 4F.

I did not apply the V-Go directly after filling. Do I have to throw it away?

It is preferable to apply the V-Go immediately after filling. However, refer to the V-Go storage conditions in Section 4 and the specific insulin’s storage conditions for more information.

I believe an item is missing or appears to be damaged.

If you suspect an item is damaged, do not use the damaged piece. Replace this with a new one (V-Go or EZ Fill). EZ Fill replacements can be requested from a Valeritas Customer Care Representative at 1-866-881-1209.

I believe I have broken the EZ Fill. How do I get another one to fill the V-Go™?

EZ Fill replacements can be requested from a Valeritas Customer Care Representative at 1-866-881-1209. You will be asked to return the unusable EZ Fill. Valeritas Customer Care will provide you with further details.

The inner package for the V-Go is torn or damaged.

If you suspect the package containing the V-Go has been torn or damaged, do not use this V-Go. Replace with a new V-Go.

After I removed the button cover, the cover pin was not attached to the button cover and is still inside the V-Go.

If the cover pin is inside the V-Go, the V-Go will not work correctly. Try to remove the pin manually; otherwise discard this V-Go and start over with a new V-Go.

It is difficult to press down on the needle button.

Be sure you are pressing the raised bump of the needle button. If the needle button does not move when pressed, the needle button may have already been activated. Do not use this V-Go. Replace with a new V-Go.

The needle button will not stay in the down position.

The needle button must be pressed down fully to be locked into place. If you cannot get the button to stay down, do not use this V-Go. Replace with a new V-Go.

The V-Go won’t remain securely attached to my skin for the duration of use, which sometimes causes poking of the needle.

If the V-Go will not remain secure, replace with a new V-Go.

When replacing the V-Go, please review Section 2 (Part 3) Step 3A to 3D.

Do not touch the adhesive pad before you attach the V-Go to your skin. Thoroughly clean the site with an alcohol swab. Let the site dry before attaching the V-Go. Many lotions and ointments may keep the V-Go from sticking to your skin.

Be sure that you have properly attached the V-Go to a flat surface on your body.

If the site is covered with hair, this could also affect whether the V-Go sticks. You may shave the area to help the V-Go attach to your skin.

When I went to give myself a bolus dose of insulin, the bolus delivery button was already popped out.

If the bolus delivery button was already popped out, the bolus ready button was already activated. Press the bolus delivery button to deliver 2 Units of insulin when the next bolus dose is needed.

The bolus delivery button will not pop out.

First check that you are pressing the bolus ready button fully. If the bolus delivery button fails to pop out after you activate the bolus ready button, you have used all of the available insulin for bolus dosing (36 Units or 18 uses per 24 hours). Replace this V-Go with a new V-Go before your next meal. Plan your day so that you have enough insulin for each meal.

What should I do if I forget the number of Units I have delivered when bolus dosing or if I forget to take a bolus dose?

Follow the plan you created with your doctor or healthcare professional for such situations. If you have not created a plan already, consult your doctor or healthcare professional for guidance.

The area of skin around the V-Go is red and sore to the touch.

Skin may be irritated by the adhesive pad on the V-Go. There are a number of skin barrier products available to help prevent irritation and treat sensitivity problems. Contact your doctor or healthcare professional for specific products and recommendations.

Infections at the site may also occur. If you experience redness, irritation, or inflammation around the V-Go (specifically the end closest to the needle), immediately replace the V-Go with a new V-Go on a new body site. Contact your doctor or healthcare professional for the best way to treat infection and irritation, especially if the inflamed site appears bigger than a dime.

I dropped the V-Go™.

Check to see if there is any damage to the V-Go. If you suspect that the V-Go was damaged or became dirty as a result of the fall, do not use this one. Replace with a new V-Go.

I dropped the EZ Fill.

Check to see if there is any damage to the EZ Fill or the insulin vial, if it was attached. If the insulin vial came out of the EZ Fill, wipe the top of the vial with an alcohol swab and watch closely for leaks when you place the vial back into the EZ Fill. If insulin is leaking, replace the insulin vial with a new one. If you suspect that the EZ Fill was damaged, speak to a Valeritas Customer Care Representative at 1-866-881-1209.

The V-Go was exposed to water. Is this a problem?

The V-Go can go under water up to 3 feet, 3 inches (1 meter), and will continue to work safely. You should check to see that it stays in place. Depending on the cleanliness of the water, you may be at an increased risk for an infection at the needle infusion site.

Can I swim, scuba dive, shower, or bathe while wearing the V-Go?

The V-Go has been successfully tested in water to depths of 3 feet, 3 inches (1 meter) for 24 hours, and therefore can be worn during normal daily activities, such as showering and bathing as well as activities near the surface of the water, such as swimming.

The V-Go has not been tested and therefore should not be used in the following conditions:

- Water activities below 3 feet, 3 inches (1 meter), such as scuba diving.
- Extremely hot water temperatures, such as hot tubs or whirlpools.

Remove the V-Go prior to scuba diving, hot tub use, or whirlpool use, and replace with a new filled V-Go afterward.

Can I wear the V-Go for longer than 24 hours – for example, if I sleep an extra hour on the weekend?

The V-Go has been designed for 24-hour wear. You should change it at the same time each day. After 24 hours, the V-Go may no longer deliver a continuous preset basal rate of insulin.

How do I travel with the V-Go?

Use the same precautions that you would when traveling with other insulin supplies. Speak with your doctor or healthcare professional about extra precautions you may need to take while traveling.

When traveling with the EZ Fill, with an insulin vial attached, it should be refrigerated at all times. Empty V-Go devices do not require refrigeration. They should be stored according to the storage conditions in Section 4. For information on storing filled V-Go devices refer to the V-Go storage conditions in Section 4.

Can I wear the V-Go on an airplane?

Yes, the V-Go can safely be worn on an airplane.

Should I wear the V-Go to bed?

Yes, you should wear the V-Go for a full 24 hours, even while you sleep.

The needle will not retract back into the V-Go.

Try to slide and press the needle release button again. See Section 2 (Part 3) Step 8C. If the needle still will not retract into the V-Go, dispose of the V-Go in a sharps container.

SECTION 7: GLOSSARY AND PACKAGING SYMBOLS

Aseptic technique: This process helps keep the V-Go™ and EZ Fill devices clean during preparation, filling, and application. Following this technique requires handwashing and wiping the application site with an alcohol swab. It may involve wiping the V-Go device with an alcohol swab if the device comes into contact with anything else.

Basal rate: The basal rate is the amount of insulin delivered at a preset rate by the V-Go over 24 hours. Your basal rate is the amount of insulin required to maintain your target glucose values when you are not eating. Basal rate may also be referred to as background, continuous, or long-acting insulin.

Blood glucose levels: Blood glucose levels are the measure of how much sugar is in the blood.

Bolus: A bolus is an amount of insulin delivered at one time. A bolus is usually taken before a meal to cover your body's insulin needs. A bolus of insulin can also be taken when blood glucose levels are abnormally high. Bolus may also be referred to as mealtime, prandial, short-acting, or rapid-acting insulin.

Diabetes mellitus: Diabetes is a disease in which the body cannot maintain its own healthy blood glucose levels. Either the body cannot produce enough insulin or the body cannot properly use insulin. There are two main types of diabetes:

Type 1 diabetes: In Type 1 diabetes, the body does not produce enough insulin. People with Type 1 diabetes must use insulin to regulate their blood glucose levels.
Type 2 diabetes: In Type 2 diabetes, the body does not produce enough insulin or use it properly. People with Type 2 diabetes can usually regulate their blood glucose levels by following an individual meal plan, exercising, and taking certain medicines, including insulin, if needed. It usually occurs in people 40 years or older.

Diabetic ketoacidosis (DKA): DKA occurs when the blood glucose level is elevated and the insulin level is low. The body does not have enough insulin to help the glucose enter the cells. Glucose in the cells is used for energy. During this situation, the body begins to burn muscle and fat for energy. A waste product of fat burning is ketones. Ketones accumulate in the blood and are passed through the urine and lungs. This condition can be identified by urine and/or blood tests. DKA usually requires hospitalization and can lead to a life-threatening situation if not promptly treated.

Glucose: Glucose, a sugar, is a main way the body takes in carbohydrates. Glucose is the body’s most important source of energy. It is produced from digested food, by the normal action of the liver. Glucose is carried by the blood throughout the body.

Hyperglycemia: Hyperglycemia or high blood sugar occurs when blood glucose levels rise above normal (approximately 250 mg/dL). Hyperglycemia is the result of the body not having enough insulin or not being able to use insulin to process glucose.

Hypoglycemia: Hypoglycemia or low blood sugar occurs when blood glucose levels drop below normal (approximately 70 mg/dL). Hypoglycemia may result from too much insulin and/or exercising more than usual.

Infusion site: The infusion site is the place on the body where the V-Go is attached, specifically the end of the V-Go where the needle is inserted under the skin.

Insulin: Insulin is a hormone produced by the pancreas. Insulin is needed by the body to regulate the production and use of glucose.

Ketones: Ketones, or ketone bodies, are substances produced by normal liver activity, and used by muscle tissue. When blood glucose levels are elevated, the body's normal process is unbalanced and ketones can accumulate in the blood, pass through the urine, and ultimately result in diabetic ketoacidosis (DKA).

Subcutaneous: Subcutaneous means beneath the layer of the skin. The V-Go infusion needle delivers insulin subcutaneously. Subcutaneous injections are not the same thing as intravenous (IV) or intramuscular (IM) injections.

Packaging Symbols

Rx Only

Store at

Unless opened or damaged, contents are sterile

Do not reuse

Dispose of after 30 fills

Use by

Before using contents, read the Instructions for Patient Use

Lot code

Humalog is a registered trademark of Eli Lilly and Company.
NovoLog is a registered trademark of Novo Nordisk A/S.

V-Go
DISPOSABLE INSULIN DELIVERY
www.go-vgo.com

valeritas
www.valeritas.com

ART-037 Rev: H
09/2011
© 2011 Valeritas, Inc.

V-Go 20 Commercial Kit

8560-9400-03

V-Go™
DISPOSABLE INSULIN DELIVERY

20

Kit Contents:

- Thirty (30) sterile, nonpyrogenic, single-use devices to be used over 24 hours (nonreusable)
- One (1) sterile, nonpyrogenic filling device designed for 30 fills with one (1) plug and one (1) cap
- One (1) V-Go Instructions for Patient Use insert
- One (1) V-Go Quick Reference Guide insert

Insulin is not included in this kit.

Dispense as one (1) kit. Do not break apart.

PHARMACIST

Dispense two (2) vials of fast-acting insulin [See Instructions for Patient Use (Section 3) for insulins tested with the V-Go] with the V-Go 20
Patient counseling materials included in kit

1-866-881-1209
www.go-vgo.com

valeritas

V-Go 30 Commercial Kit

8560-9400-02

V-Go™
DISPOSABLE INSULIN DELIVERY

30

Kit Contents:

- Thirty (30) sterile, nonpyrogenic, single-use devices to be used over 24 hours (nonreusable)
- One (1) sterile, nonpyrogenic filling device designed for 30 fills with one (1) plug and one (1) cap
- One (1) V-Go Instructions for Patient Use insert
- One (1) V-Go Quick Reference Guide insert

Insulin is not included in this kit.

Dispense as one (1) kit. Do not break apart.

PHARMACIST

Dispense three (3) vials of fast-acting insulin [See Instructions for Patient Use (Section 3) for insulins tested with the V-Go] with the V-Go 30
Patient counseling materials included in kit

1-866-881-1209
www.go-vgo.com

valeritas

V-Go 40 Commercial Kit

8560-9400-01

V-Go™
DISPOSABLE INSULIN DELIVERY

40

Kit Contents:

- Thirty (30) sterile, nonpyrogenic, single-use devices to be used over 24 hours (nonreusable)
- One (1) sterile, nonpyrogenic filling device designed for 30 fills with one (1) plug and one (1) cap
- One (1) V-Go Instructions for Patient Use insert
- One (1) V-Go Quick Reference Guide insert

Insulin is not included in this kit.

Dispense as one (1) kit. Do not break apart.

PHARMACIST

Dispense three (3) vials of fast-acting insulin [See Instructions for Patient Use (Section 3) for insulins tested with the V-Go] with the V-Go 40
Patient counseling materials included in kit

1-866-881-1209
www.go-vgo.com

valeritas